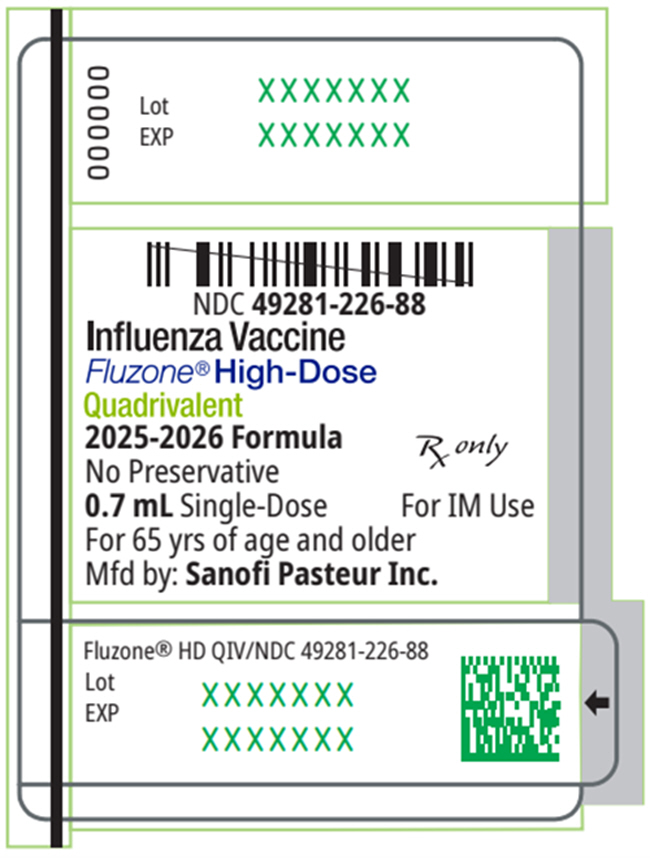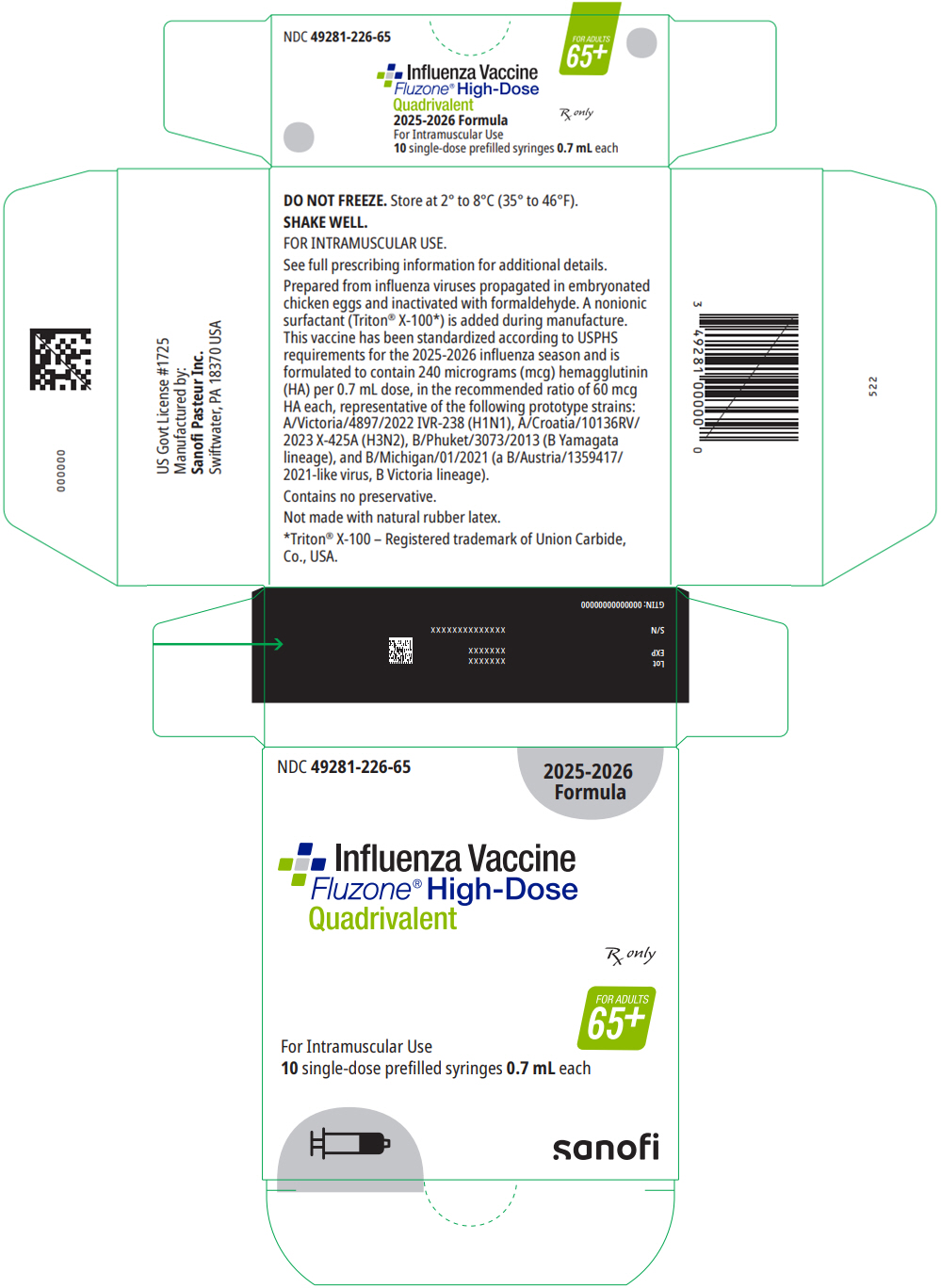 DRUG LABEL: Fluzone High-Dose Quadrivalent Northern Hemisphere
NDC: 49281-226 | Form: INJECTION, SUSPENSION
Manufacturer: Sanofi Pasteur Inc.
Category: other | Type: VACCINE LABEL
Date: 20250711

ACTIVE INGREDIENTS: INFLUENZA A VIRUS A/VICTORIA/4897/2022 IVR-238 (H1N1) ANTIGEN (FORMALDEHYDE INACTIVATED) 60 ug/0.7 mL; INFLUENZA A VIRUS A/CROATIA/10136RV/2023 X-425A (H3N2) ANTIGEN (FORMALDEHYDE INACTIVATED) 60 ug/0.7 mL; INFLUENZA B VIRUS B/PHUKET/3073/2013 ANTIGEN (FORMALDEHYDE INACTIVATED) 60 ug/0.7 mL; INFLUENZA B VIRUS B/MICHIGAN/01/2021 ANTIGEN (FORMALDEHYDE INACTIVATED) 60 ug/0.7 mL
INACTIVE INGREDIENTS: GELATIN, UNSPECIFIED; SODIUM PHOSPHATE, DIBASIC, ANHYDROUS; SODIUM PHOSPHATE, MONOBASIC, ANHYDROUS; WATER; OCTOXYNOL-9; FORMALDEHYDE

HIGHLIGHTS OF PRESCRIBING INFORMATION

These highlights do not include all the information needed to use Fluzone® High-Dose Quadrivalent safely and effectively. See full prescribing information for Fluzone High-Dose Quadrivalent.
Fluzone High-Dose Quadrivalent (Influenza Vaccine)
injectable suspension, for intramuscular use
2025-2026 Formula
Initial U.S. Approval: 2019

1 INDICATIONS AND USAGE

Fluzone High-Dose Quadrivalent is a vaccine indicated for active immunization for the prevention of disease caused by influenza A subtype viruses and type B viruses contained in the vaccine. (1)

Fluzone High-Dose Quadrivalent is approved for use in persons 65 years of age and older. (1)

2 DOSAGE AND ADMINISTRATION

For intramuscular use

Administer Fluzone High-Dose Quadrivalent as a single 0.7 mL dose. (2)

3 DOSAGE FORMS AND STRENGTHS

Fluzone High-Dose Quadrivalent is an injectable suspension. A single dose is 0.7 mL (3)

4 CONTRAINDICATIONS

Do not administer Fluzone High-Dose Quadrivalent to anyone with a history of severe allergic reaction (e.g., anaphylaxis) to any component of the vaccine, including egg protein, or to a previous dose of any influenza vaccine (4, 11)

5 WARNINGS AND PRECAUTIONS

If Guillain-Barré Syndrome (GBS) has occurred within 6 weeks following previous influenza vaccination, the decision to give Fluzone High-Dose Quadrivalent should be based on careful consideration of the potential benefits and risks. (5.1)

6 ADVERSE REACTIONS

In adults ≥65 years of age, the most common (>10%) injection-site adverse reaction was pain (41.3%); the most common solicited systemic adverse reactions were myalgia (22.7%), headache (14.4%) and malaise (13.2%). (6.1)

To report SUSPECTED ADVERSE REACTIONS, contact Sanofi Pasteur Inc., Discovery Drive, Swiftwater, PA 18370 at 1-800-822-2463 (1-800-VACCINE) or VAERS at 1-800-822-7967 or https://vaers.hhs.gov.

FULL PRESCRIBING INFORMATION

1 INDICATIONS AND USAGE

Fluzone® High-Dose Quadrivalent is a vaccine indicated for active immunization for the prevention of disease caused by influenza A subtype viruses and type B viruses contained in the vaccine.

Fluzone High-Dose Quadrivalent is indicated for use in persons 65 years of age and older.

2 DOSAGE AND ADMINISTRATION

For intramuscular use

2.1 Dose and Schedule

Administer Fluzone High-Dose Quadrivalent as a single 0.7 mL dose.

2.2 Administration

Fluzone High-Dose Quadrivalent is a colorless opalescent liquid. Parenteral drug products should be inspected visually for particulate matter and discoloration prior to administration, whenever solution and container permit. If either of these conditions exist, the vaccine should not be administered.

Before administering a dose of vaccine, shake the prefilled syringe.

Administer Fluzone High-Dose Quadrivalent intramuscularly.

3 DOSAGE FORMS AND STRENGTHS

Fluzone High-Dose Quadrivalent is an injectable suspension.

A single dose is 0.7 mL.

4 CONTRAINDICATIONS

Do not administer Fluzone High-Dose Quadrivalent to anyone with a history of severe allergic reaction (e.g., anaphylaxis) to any component of the vaccine [see Description (11)], including egg protein, or to a previous dose of any influenza vaccine.

5 WARNINGS AND PRECAUTIONS

5.1 Guillain-Barré Syndrome

If Guillain-Barré Syndrome (GBS) has occurred within 6 weeks following any previous influenza vaccination, the decision to give Fluzone High-Dose Quadrivalent should be based on careful consideration of the potential benefits and risks.

The 1976 swine influenza vaccine was associated with an elevated risk of GBS. Evidence for a causal relation of GBS with other influenza vaccines is inconclusive; if an excess risk exists, it is probably slightly more than 1 additional case per 1 million persons vaccinated. (See reference 1.)

5.2 Preventing and Managing Allergic Reactions

Appropriate medical treatment must be immediately available to manage potential anaphylactic reactions following administration of the vaccine.

5.3 Altered Immunocompetence

If Fluzone High-Dose Quadrivalent is administered to immunocompromised persons, including those receiving immunosuppressive therapy, the immune response may be lower than expected.

5.4 Limitations of Vaccine Effectiveness

Vaccination with Fluzone High-Dose Quadrivalent may not protect all recipients.

5.5 Syncope

Syncope (fainting) has been reported following vaccination with Fluzone High-Dose Quadrivalent. Procedures should be in place to avoid injury from fainting.

6 ADVERSE REACTIONS

In adults ≥65 years of age, the most common (>10%) injection-site adverse reaction was pain (41.3%); the most common solicited systemic adverse reactions were myalgia (22.7%), headache (14.4%) and malaise (13.2%).

6.1 Clinical Trials Experience

Because clinical trials are conducted under widely varying conditions, adverse event rates observed in the clinical trial(s) of a vaccine cannot be directly compared to rates in the clinical trial(s) of another vaccine and may not reflect the rates observed in practice. One clinical study has evaluated the safety of Fluzone High-Dose Quadrivalent.

Study 1 (NCT03282240) was a randomized, active-controlled, modified double-blind pre-licensure trial conducted in the U.S. The study compared the safety and immunogenicity of Fluzone High-Dose Quadrivalent to those of Fluzone High-Dose (trivalent formulation). The safety analysis set included 1777 Fluzone High-Dose Quadrivalent recipients, 443 Fluzone High-Dose recipients, and 450 investigational Fluzone High-Dose containing the alternate B influenza strain recipients.

The most common reactions occurring after Fluzone High-Dose Quadrivalent administration were injection-site pain (41.3%), myalgia (22.7%), headache (14.4%), and malaise (13.2%). Onset usually occurred within the first 3 days after vaccination. The majority of solicited reactions resolved within three days of vaccination.

Table 1 displays solicited adverse reactions for Fluzone High-Dose Quadrivalent compared to Fluzone High-Dose reported within 7 days after vaccination and collected using standardized diary cards.

Table 1: Frequency of Solicited Injection-Site Systemic Adverse Reactions within 7 Days after Vaccination with Fluzone High-Dose Quadrivalent or Fluzone High-Dose, Adults 65 Years of Age and Older (Study 1 [NCT03282240])
 | Fluzone High-Dose Quadrivalent (N [N is the number of vaccinated participants with available data for the events listed] =1761-1768) |  | Fluzone High-Dose [Safety results for the Fluzone High-Dose and investigational Fluzone High-Dose containing the alternate B influenza strain recipients were pooled for the analysis.] (N=885-889)
 | Percentage |  | Percentage
 | Any | Grade 3 | Any | Grade 3
Local Reactions
Injection Site Pain [Grade 3: A type of AE that interrupts usual activities of daily living, or significantly affects clinical status, or may require intensive therapeutic intervention.] | 41.3 | 0.7 | 36.4 | 0.2
Injection Site Erythema [Grade 3: > 100 mm] | 6.2 | 0.6 | 5.7 | 0.2
Injection Site Swelling | 4.9 | 0.3 | 4.7 | 0.1
Injection Site Induration | 3.7 | 0.2 | 3.5 | 0.1
Injection Site Bruising | 1.3 | 0.0 | 1.1 | 0.0
Systemic Reactions
Myalgia | 22.7 | 0.9 | 18.9 | 0.7
Headache | 14.4 | 0.6 | 13.6 | 0.4
Malaise | 13.2 | 0.7 | 13.4 | 0.4
Shivering | 5.4 | 0.3 | 4.7 | 0.3
Fever [Grade 3: ≥ 102.1°F (39.0°C)] | 0.4 | 0.2 | 0.9 | 0.2

Based on data from Fluzone High-Dose, solicited injection site reactions and systemic adverse reactions were slightly more frequent after vaccination with Fluzone High-Dose compared to a standard-dose vaccine.

Unsolicited non-serious adverse events were reported in 279 (15.7%) recipients in the Fluzone High-Dose Quadrivalent group and 140 (15.7%) recipients in the Fluzone High-Dose group. The most commonly reported unsolicited adverse event was cough.

Within 180 days post-vaccination, 80 (4.5%) Fluzone High-Dose Quadrivalent recipients and 48 (5.4%) Fluzone High-Dose recipients experienced a serious adverse event (SAE). None of the SAEs were assessed as related to the study vaccines.

6.2 Postmarketing Experience

The following additional adverse events have been spontaneously reported during the postmarketing use of Fluzone High-Dose, Fluzone, Fluzone Quadrivalent, or Fluzone High-Dose Quadrivalent. Because these events are reported voluntarily from a population of uncertain size, it is not always possible to reliably estimate their frequency or establish a causal relationship to vaccine exposure. Adverse events were included based on one or more of the following factors: severity, frequency of reporting, or strength of evidence for a causal relationship to Fluzone High-Dose, Fluzone Fluzone Quadrivalent or Fluzone High-Dose Quadrivalent.

- Blood and Lymphatic System Disorders: Thrombocytopenia, lymphadenopathy
- Immune System Disorders: Anaphylaxis, other allergic/hypersensitivity reactions (including urticaria, angioedema)
- Eye Disorders: Ocular hyperemia
- Nervous System Disorders: Guillain-Barré syndrome (GBS), convulsions, febrile convulsions, myelitis (including encephalomyelitis and transverse myelitis), facial palsy (Bell's palsy), optic neuritis/neuropathy, brachial neuritis, syncope (shortly after vaccination), dizziness, paresthesia
- Vascular Disorders: Vasculitis, vasodilatation
- Respiratory, Thoracic and Mediastinal Disorders: Dyspnea, cough, wheezing, throat tightness, oropharyngeal pain, and rhinorrhea
- Gastrointestinal Disorders: Vomiting
- Skin and Subcutaneous Tissue Disorders: Stevens-Johnson syndrome
- General Disorders and Administration Site Conditions: pruritus, asthenia/fatigue, chest pain, chills

8 USE IN SPECIFIC POPULATIONS

8.1 Pregnancy

Fluzone High-Dose Quadrivalent is not approved for use in persons <65 years of age. There are no human or animal data available on Fluzone High-Dose Quadrivalent to establish whether there is a vaccine-associated risk with use of Fluzone High-Dose Quadrivalent in pregnancy.

8.2 Lactation

Fluzone High-Dose Quadrivalent is not approved for use in persons <65 years of age. No human or animal data are available to assess the effects of Fluzone High-Dose Quadrivalent on the breastfed infant or on milk production/excretion.

8.4 Pediatric Use

Safety and effectiveness of Fluzone High-Dose Quadrivalent in children younger than 18 years of age have not been established.

8.5 Geriatric Use

Safety, immunogenicity, and efficacy of Fluzone High-Dose Quadrivalent have been evaluated in adults 65 years of age and older [see Adverse Reactions (6.1) and Clinical Studies (14)].

11 DESCRIPTION

Fluzone High-Dose Quadrivalent for intramuscular use is an inactivated influenza vaccine, prepared from influenza viruses propagated in embryonated chicken eggs. The virus-containing allantoic fluid is harvested and inactivated with formaldehyde. Influenza virus is concentrated and purified in a linear sucrose density gradient solution using a continuous flow centrifuge. The virus is then chemically disrupted using a non-ionic surfactant, octylphenol ethoxylate (Triton® X-100), producing a "split virus." The split virus containing hemagglutinin (HA) antigen is further purified and then suspended in sodium phosphate-buffered isotonic sodium chloride solution. The Fluzone High-Dose Quadrivalent process uses an additional concentration factor after the ultrafiltration step in order to obtain a higher HA antigen concentration. The purified split virus from the four strains included in the vaccine are produced separately and then combined to make the quadrivalent formulation.

Fluzone High-Dose Quadrivalent is an injectable suspension and is a colorless opalescent liquid.

Neither antibiotics nor preservative are used in the manufacture of Fluzone High-Dose Quadrivalent.

The Fluzone High-Dose Quadrivalent prefilled syringe presentation is not made with natural rubber latex.

Fluzone High-Dose Quadrivalent is standardized according to United States Public Health Service requirements and is formulated to contain HA of each of the following four influenza strains recommended for the 2025-2026 influenza season: A/Victoria/4897/2022 IVR-238 (H1N1), A/Croatia/10136RV/2023 X-425A (H3N2), B/Phuket/3073/2013 (B Yamagata lineage), and B/Michigan/01/2021 (a B/Austria/1359417/2021-like virus, B Victoria lineage).

The amounts of HA and other ingredients per dose of vaccine are listed in Table 2.

Table 2: Fluzone High-Dose Quadrivalent Ingredients
Ingredient | Quantity (per dose)
Ingredient | Fluzone High-Dose Quadrivalent 0.7 mL Dose
Active Substance: Split influenza virus, inactivated strains [per United States Public Health Service (USPHS) requirement] : | 240 mcg HA total
A (H1N1) | 60 mcg HA
A (H3N2) | 60 mcg HA
B (Victoria Lineage) | 60 mcg HA
B (Yamagata Lineage) | 60 mcg HA
Other:
Sodium phosphate-buffered isotonic sodium chloride solution | QS [Quantity sufficient] to appropriate volume
Formaldehyde | ≤140 mcg
Octylphenol ethoxylate | ≤350 mcg
Gelatin | None
Preservative | None

12 CLINICAL PHARMACOLOGY

12.1 Mechanism of Action

Specific levels of hemagglutination inhibition (HI) antibody titer post-vaccination with inactivated influenza virus vaccines have not been correlated with protection from influenza virus infection. In some human studies, antibody titers ≥1:40 have been associated with protection from influenza illness in up to 50% of participants. (See references 2 and 3.)

Antibodies against one influenza virus type or subtype confer limited or no protection against another. Furthermore, antibodies to one antigenic variant of influenza virus might not protect against a new antigenic variant of the same type or subtype. Frequent development of antigenic variants through antigenic drift is the virologic basis for seasonal epidemics and the reason for the usual change of one or more new strains in each year's influenza vaccine.

13 NONCLINICAL TOXICOLOGY

Carcinogenesis, Mutagenesis, Impairment of Fertility

Fluzone High-Dose Quadrivalent has not been evaluated for carcinogenic or mutagenic potential or for impairment of fertility.

14 CLINICAL STUDIES

14.1 Immunogenicity of Fluzone High-Dose Quadrivalent in Adults 65 Years of Age and Older

Study 1 (NCT03282240, see http://clinicaltrials.gov) was a randomized, active-controlled, modified double-blind trial in adults 65 years of age and older conducted in the US. The study compared the safety and immunogenicity of Fluzone High-Dose Quadrivalent to those of Fluzone High-Dose. The objective was to demonstrate immunologic non-inferiority of Fluzone High-Dose Quadrivalent to Fluzone High-Dose, as assessed by HAI geometric mean antibody titers (GMTs) at Day 28 and seroconversion rates, to strains common to formulations of both vaccines, based on pre-specified criteria.

A total of 2670 adults from 65 years of age were randomized (4:1:1) to receive one dose of either Fluzone High-Dose Quadrivalent or one of two formulations of Fluzone High-Dose (one formulation contained a B strain of the Victoria lineage [TIV-HD1] while the other contained a B strain of the Yamagata lineage [TIV-HD2]).

Females accounted for 58.2% of participants in the Fluzone High-Dose Quadrivalent group and 57.4% of participants in the Fluzone High-Dose group (TIV-HD1 and TIV-HD2, pooled). The mean age was 72.9 years (range: 65 through 100 years) in the Fluzone High-Dose Quadrivalent group and the mean age was 73.0 (range: 65 through 95 years) in the Fluzone High-Dose group. The percentage of subjects 75 years of age or older was 35.4% in the Fluzone High-Dose Quadrivalent group and 35.8% in the Fluzone High-Dose group. Most participants were White (91.2% and 89.7%), followed by Black (6.8% and 8.0%), and Hispanic (2.8% and 2.6%) in the Fluzone High-Dose Quadrivalent and Fluzone High-Dose groups, respectively.

The immunogenicity results of Study 1 are summarized in Table 3 and Table 4 below.

Table 3: Post-vaccination HAI Antibody GMTs and Analyses of Non-inferiority of Fluzone High-Dose Quadrivalent Relative to Fluzone High-Dose, Adults 65 Years of Age and Older, Per-Protocol Analysis Set (Study 1 [NCT03282240])
Influenza Strain | GMT |  |  | GMT Ratio | Met Predefined Non-inferiority Criteria [Predefined noninferiority criterion for the GMT ratio: the lower limit of the 95% CI of the GMT ratio (QIV-HD divided by TIV-HD) is >0.667]
Influenza Strain | QIV-HD | TIV-HD1 [TIV-HD1 contained A/Michigan/45/2015 (H1N1), A/Hong Kong/4801/2014 (H3N2), and B/Brisbane/60/2008 (B1, Victoria lineage)] (B1 Victoria) | TIV-HD2 [TIV-HD2 contained A/Michigan/45/2015 (H1N1), A/Hong Kong/4801/2014 (H3N2), and B/Phuket/3073/2013 (B2, Yamagata lineage)] (B2 Yamagata) | QIV-HD over TIV-HD (95% CI) | Met Predefined Non-inferiority Criteria [Predefined noninferiority criterion for the GMT ratio: the lower limit of the 95% CI of the GMT ratio (QIV-HD divided by TIV-HD) is >0.667]
Influenza Strain | N [N is the number of vaccinated participants with available data for the immunologic endpoint listed] =1679-1680 | N=423 | N=430 | QIV-HD over TIV-HD (95% CI) | Met Predefined Non-inferiority Criteria [Predefined noninferiority criterion for the GMT ratio: the lower limit of the 95% CI of the GMT ratio (QIV-HD divided by TIV-HD) is >0.667]
A (H1N1) [Pooled TIV-HD group includes subjects vaccinated with either TIV-HD1 or TIV-HD2 for the A strain comparison] | 312 | 374 |  | 0.83 (0.744; 0.932) | Yes
A (H3N2) | 563 | 594 |  | 0.95 (0.842; 1.066) | Yes
B1 (Victoria) | 516 | 476 | -- | 1.08 (0.958; 1.224) | Yes
B2 (Yamagata) | 578 | -- | 580 | 1.00 (0.881; 1.129) | Yes

Table 4: Seroconversion Rates and Analyses of Non-inferiority of Fluzone High-Dose Quadrivalent Relative to Fluzone High-Dose, Adults 65 Years of Age and Older, Per-Protocol Analysis Set (Study 1 [NCT03282240])
Influenza Strain | Seroconversion Rates (Percentage) [Seroconversion Rates: For subjects with a pre-vaccination titer <10 (1/dil), proportion of subjects with a post-vaccination titer ≥40 (1/dil) and for subjects with a pre-vaccination titer ≥10 (1/dil), proportion of subjects with a ≥four-fold increase from pre-vaccination to post-vaccination titer] |  |  | Difference of Seroconversion Rates | Met Predefined Non-inferiority Criteria [Predefined noninferiority criterion for seroconversion: the lower limit of the two-sided 95% CI of the difference of the seroconversion rates (QIV-HD minus TIV-HD) is >-10%]
Influenza Strain | QIV-HD | TIV-HD1 [TIV-HD1 contained A/Michigan/45/2015 (H1N1), A/Hong Kong/4801/2014 (H3N2), and B/Brisbane/60/2008 (B1, Victoria lineage)] (B1 Victoria) | TIV-HD2 [TIV-HD2 contained A/Michigan/45/2015 (H1N1), A/Hong Kong/4801/2014 (H3N2), and B/Phuket/3073/2013 (B2, Yamagata lineage)] (B2 Yamagata) | QIV-HD minus TIV-HD (95% CI) | Met Predefined Non-inferiority Criteria [Predefined noninferiority criterion for seroconversion: the lower limit of the two-sided 95% CI of the difference of the seroconversion rates (QIV-HD minus TIV-HD) is >-10%]
Influenza Strain | N [N is the number of vaccinated participants with available data for the immunologic endpoint listed] =1668-1669 | N=420-421 | N=428 | QIV-HD minus TIV-HD (95% CI) | Met Predefined Non-inferiority Criteria [Predefined noninferiority criterion for seroconversion: the lower limit of the two-sided 95% CI of the difference of the seroconversion rates (QIV-HD minus TIV-HD) is >-10%]
A (H1N1) [Pooled TIV-HD group includes subjects vaccinated with either TIV-HD1 or TIV-HD2 for the A strain comparison] | 50.4 | 53.7 |  | -3.27 (-7.37; 0.86) | Yes
A (H3N2) | 49.8 | 50.5 |  | -0.71 (-4.83; 3.42) | Yes
B1 (Victoria) | 36.5 | 39.0 | -- | -2.41 (-7.66; 2.70) | Yes
B2 (Yamagata) | 46.6 | -- | 48.4 | -1.75 (-7.04; 3.53) | Yes

Fluzone High-Dose Quadrivalent was as immunogenic as Fluzone High-Dose for GMTs and seroconversion rates for the common influenza strains. Fluzone High-Dose Quadrivalent induced a superior immune response, based on a pre-specified superiority criterion, with respect to the additional B strain than the immune response induced by Fluzone High-Dose formulation that did not contain the additional B strain.

14.2 Efficacy of Fluzone High-Dose in Adults 65 Years of Age and Older

The efficacy of Fluzone High-Dose (trivalent formulation) is relevant to Fluzone High-Dose Quadrivalent since both vaccines are manufactured according to the same process and have overlapping compositions.

Study 2 (NCT01427309) was a multi-center, double-blind, post-licensure efficacy trial conducted in the U.S. and Canada in which adults 65 years of age and older were randomized (1:1) to receive either Fluzone High-Dose or Fluzone. The study was conducted over two influenza seasons (2011-2012 and 2012-2013); 53% of participants enrolled in the first year of the study were re-enrolled and re-randomized in the second year. The per-protocol analysis set for efficacy assessments included 15,892 Fluzone High-Dose recipients and 15,911 Fluzone recipients. The majority (67%) of participants in the per-protocol analysis set for efficacy had one or more high-risk chronic comorbid conditions.

In the per-protocol analysis set, females accounted for 57.2% of participants in the Fluzone High-Dose group and 56.1% of participants in the Fluzone group. In both groups, the median age was 72.2 years (range 65 through 100 years). Overall, most participants in the study were White (95%); approximately 4% of study participants were Black, and approximately 6% reported Hispanic ethnicity.

The primary endpoint of the study was the occurrence of laboratory-confirmed influenza (as determined by culture or polymerase chain reaction) caused by any influenza viral type/subtype in association with influenza-like illness (ILI), defined as the occurrence of at least one of the following respiratory symptoms: sore throat, cough, sputum production, wheezing, or difficulty breathing; concurrent with at least one of the following systemic signs or symptoms: temperature >99.0°F, chills, tiredness, headaches or myalgia. Participants were monitored for the occurrence of a respiratory illness by both active and passive surveillance, starting 2 weeks post-vaccination for approximately 7 months. After an episode of respiratory illness, nasopharyngeal swab samples were collected for analysis; attack rates and vaccine efficacy were calculated (see Table 5).

Table 5: Relative Efficacy Against Laboratory-Confirmed Influenza [Laboratory-confirmed: culture or polymerase-chain-reaction–confirmed] Regardless of Similarity to the Vaccine Components, Associated with Influenza-Like Illness [Occurrence of at least one of the following respiratory symptoms: sore throat, cough, sputum production, wheezing, or difficulty breathing; concurrent with at least one of the following systemic signs or symptoms: temperature >99.0°F, chills, tiredness, headaches or myalgia] , Adults 65 Years of Age and Older (Study 2 [NCT01427309])
 | Fluzone High-Dose N [N is the number of vaccinated participants in the per-protocol analysis set for efficacy assessments] =15,892 n [n is the number of participants with protocol-defined influenza-like illness with laboratory confirmation] (%) | Fluzone N=15,911 n (%) | Relative Efficacy % (95% CI)
Any type/subtype [Primary endpoint] | 227 (1.43) | 300 (1.89) | 24.2 (9.7; 36.5) [The prespecified statistical superiority criterion for the primary endpoint (lower limit of the 2-sided 95% CI of the vaccine efficacy of Fluzone High-Dose relative to Fluzone >9.1%) was met.]
Influenza A | 190 (1.20) | 249 (1.56) | 23.6 (7.4; 37.1)
A (H1N1) | 8 (0.05) | 9 (0.06) | 11.0 (-159.9; 70.1)
A (H3N2) | 171 (1.08) | 222 (1.40) | 22.9 (5.4; 37.2)
Influenza B [In the first year of the study the influenza B component of the vaccine and the majority of influenza B cases were of the Victoria lineage; in the second year the influenza B component of the vaccine and the majority of influenza B cases were of the Yamagata lineage] | 37 (0.23) | 51 (0.32) | 27.4 (-13.1; 53.8)

A secondary endpoint of the study was the occurrence of culture-confirmed influenza caused by viral types/subtypes antigenically similar to those contained in the respective annual vaccine formulations in association with a modified CDC-defined ILI, defined as the occurrence of a temperature >99.0°F (>37.2°C) with cough or sore throat. The efficacy of Fluzone High-Dose relative to Fluzone for this endpoint was 51.1% (95% CI: 16.8; 72.0).

15 REFERENCES

1 Lasky T, Terracciano GJ, Magder L, et al. The Guillain-Barré syndrome and the 1992-1993 and 1993-1994 influenza vaccines. N Engl J Med 1998;339:1797-802.
2 Hannoun C, Megas F, Piercy J. Immunogenicity and protective efficacy of influenza vaccination. Virus Res 2004;103:133-138.
3 Hobson D, Curry RL, Beare AS, Ward-Gardner A. The role of serum haemagglutination-inhibiting antibody in protection against challenge infection with influenza A2 and B viruses. J Hyg Camb 1972;70:767-777.

16 HOW SUPPLIED/STORAGE AND HANDLING

16.1 How Supplied

Single-dose, prefilled syringe, without needle, 0.7 mL (NDC 49281-226-88) (not made with natural rubber latex). Supplied as package of 10 (NDC 49281-226-65).

16.2 Storage and Handling

Store Fluzone High-Dose Quadrivalent refrigerated at 2° to 8°C (35° to 46°F). DO NOT FREEZE. Discard if vaccine has been frozen.

Do not use after the expiration date shown on the label.

17 PATIENT COUNSELING INFORMATION

See FDA-approved patient labeling (Patient Information).

- Inform the patient or caregiver that Fluzone High-Dose Quadrivalent contains killed viruses and cannot cause influenza.
- Fluzone High-Dose Quadrivalent stimulates the immune system to produce antibodies that help protect against influenza.
- Instruct that annual influenza vaccination is recommended.
- Instruct vaccine recipients and caregivers to report adverse reactions to their healthcare provider and/or to Vaccine Adverse Event Reporting System (VAERS).
- Give the Vaccine Information Statements to recipients or caregivers, which are required by the National Childhood Vaccine Injury Act of 1986 prior to each immunization. These materials are available free of charge at the Centers for Disease Control and Prevention (CDC) website (www.cdc.gov/vaccines).

Fluzone is a registered trademark of Sanofi Pasteur Inc.

Manufactured by:
Sanofi Pasteur Inc.
Swiftwater, PA 18370 USA

Patient Information Sheet Fluzone® High-Dose Quadrivalent Influenza Vaccine

Please read this information sheet before getting Fluzone High-Dose Quadrivalent vaccine. This summary is not intended to take the place of talking with your healthcare provider. If you have questions or would like more information, please talk with your healthcare provider.

What is Fluzone High-Dose Quadrivalent vaccine?

Fluzone High-Dose Quadrivalent is a vaccine that helps protect against influenza illness (flu).

Fluzone High-Dose Quadrivalent vaccine is for people 65 years of age and older.

Vaccination with Fluzone High-Dose Quadrivalent vaccine may not protect all people who receive the vaccine.

Who should not get Fluzone High-Dose Quadrivalent vaccine?

You should not get Fluzone High-Dose Quadrivalent vaccine if you:

- ever had a severe allergic reaction to eggs or egg products.
- ever had a severe allergic reaction after getting any influenza vaccine.

Tell your healthcare provider if you have or have had:

- Guillain-Barré Syndrome (severe muscle weakness) after getting an influenza vaccine.
- problems with your immune system as the immune response may be diminished.

How is Fluzone High-Dose Quadrivalent vaccine given?

Fluzone High-Dose Quadrivalent vaccine is given as an injection into the muscle.

What are the possible side effects of Fluzone High-Dose Quadrivalent vaccine?

The most common side effects of Fluzone High-Dose Quadrivalent vaccine are:

- pain where you got the injection
- muscle ache
- tiredness
- headache

These are not all of the possible side effects of Fluzone High-Dose Quadrivalent vaccine. Ask your healthcare provider about other side effects.

Call your healthcare provider for advice about any side effects that concern you. You may report side effects to the Vaccine Adverse Event Reporting System (VAERS) at 1-800-822-7967 or https://vaers.hhs.gov.

Why should I get Fluzone High-Dose Quadrivalent vaccine instead of a standard-dose quadrivalent influenza vaccine?

Among persons 65 years of age and older, Fluzone High-Dose Quadrivalent generated a similar immune response to Fluzone High-Dose and is expected to provide better protection against influenza compared to standard-dose quadrivalent influenza vaccines.

What are the ingredients in Fluzone High-Dose Quadrivalent vaccine?

Fluzone High-Dose Quadrivalent vaccine contains 4 killed influenza virus strains. There is no live influenza virus in Fluzone High-Dose Quadrivalent. Fluzone High-Dose Quadrivalent cannot cause influenza.

Inactive ingredients include formaldehyde and octylphenol ethoxylate.

Manufactured by: Sanofi Pasteur Inc.
Swiftwater, PA 18370 USA

PRINCIPAL DISPLAY PANEL - 0.7 mL Syringe Label

NDC 49281-226-88

Influenza Vaccine
Fluzone® High-Dose
Quadrivalent

2025-2026 Formula
No Preservative
0.7 mL Single-Dose
For 65 yrs of age and older
Mfd by: Sanofi Pasteur Inc.

Rx only

For IM Use

PRINCIPAL DISPLAY PANEL - 0.7 mL Syringe Package

NDC 49281-226-65

FOR ADULTS
65^+

Influenza Vaccine
Fluzone® High-Dose
Quadrivalent

2025-2026 Formula
For Intramuscular Use
10 single-dose prefilled syringes 0.7 mL each

Rx only